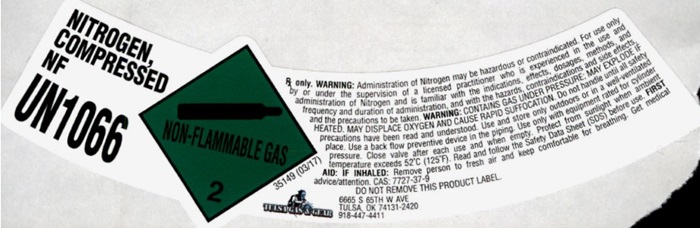 DRUG LABEL: Nitrogen
NDC: 71707-012 | Form: GAS
Manufacturer: TULSA GAS & GEAR, LLC
Category: prescription | Type: HUMAN PRESCRIPTION DRUG LABEL
Date: 20241029

ACTIVE INGREDIENTS: NITROGEN 991 mL/1 L

Nitrogen

PACKAGE LABEL

NITROGEN, COMPRESSED NF
UN1066
Rx only. WARNING: Administration of Nitrogen may be hazardous or contraindicated. For use only by or under the supervision of a licensed practitioner who is experienced in the use and administration of Nitrogen and is familiar with the indications, effects, dosages, methods, and frequency and duration of administration, and with the hazards, contraindications and side effects, and the precautions to be taken. WARNING: CONTAINS GAS UNDER PRESSURE; MAY EXPLODE IF HEATED. MAY DISPLACE OXYGEN AND CAUSE RAPID SUFFOCATION. Do not handle until all safety precautions have been read and understood. Use only with equipment rated for cylinder pressure. Close valve after each use and when empty. Protect from sunlight when ambient temperature exceeds 52 degrees C (125 degrees F). Read and follow the Safety Data Sheet (SDS) before use. FIRST AID: IF INHALED: Remove person to fresh air and keep comfortable for breathing. Get medical advice/attention. CAS: 7727-37-9
DO NOT REMOVE THIS PRODUCT LABLE.
TULSA GAS & GEAR
6665 S 65TH W AVE
TULSA, OK 74131-2420
918-447-4411